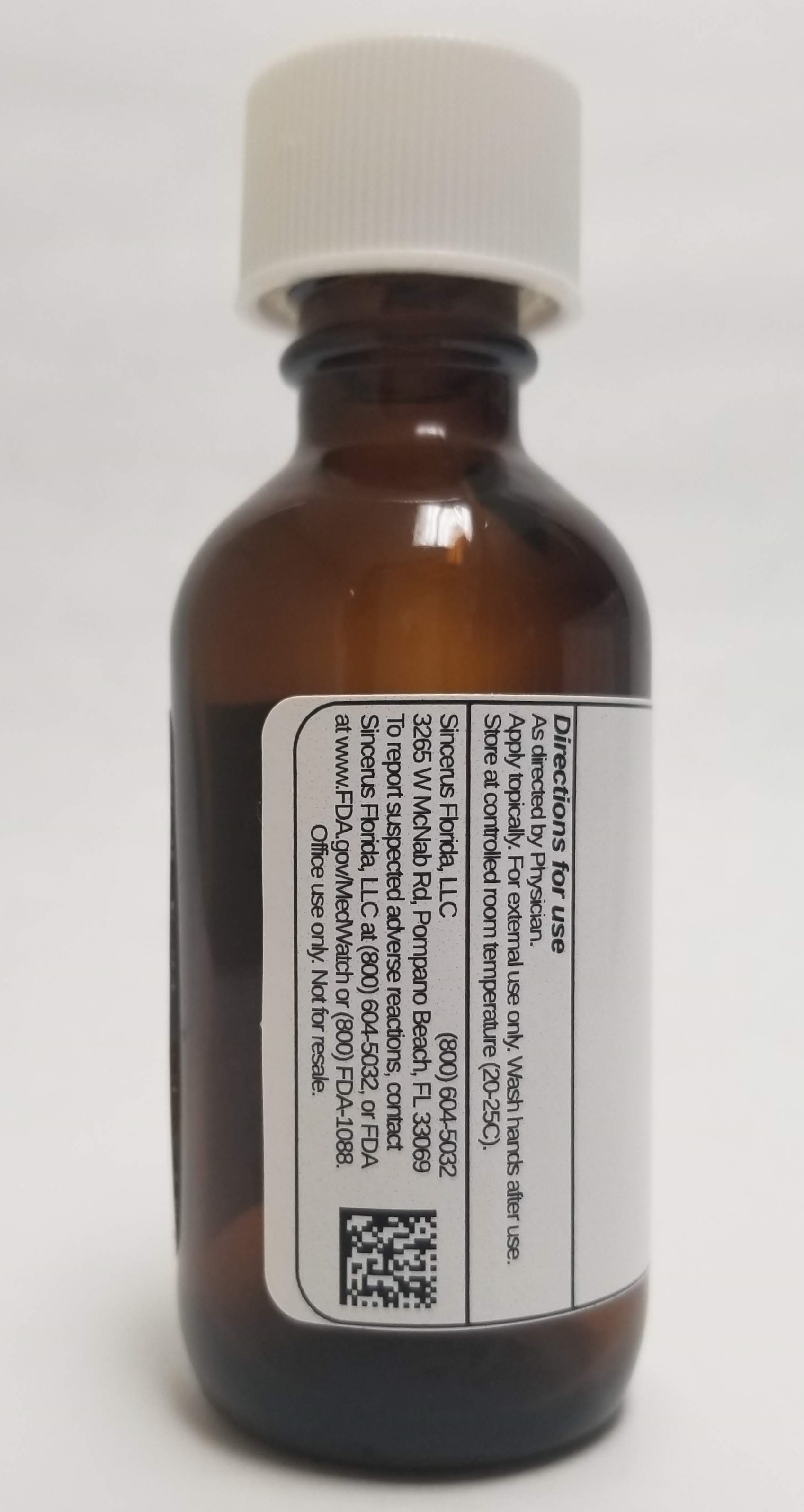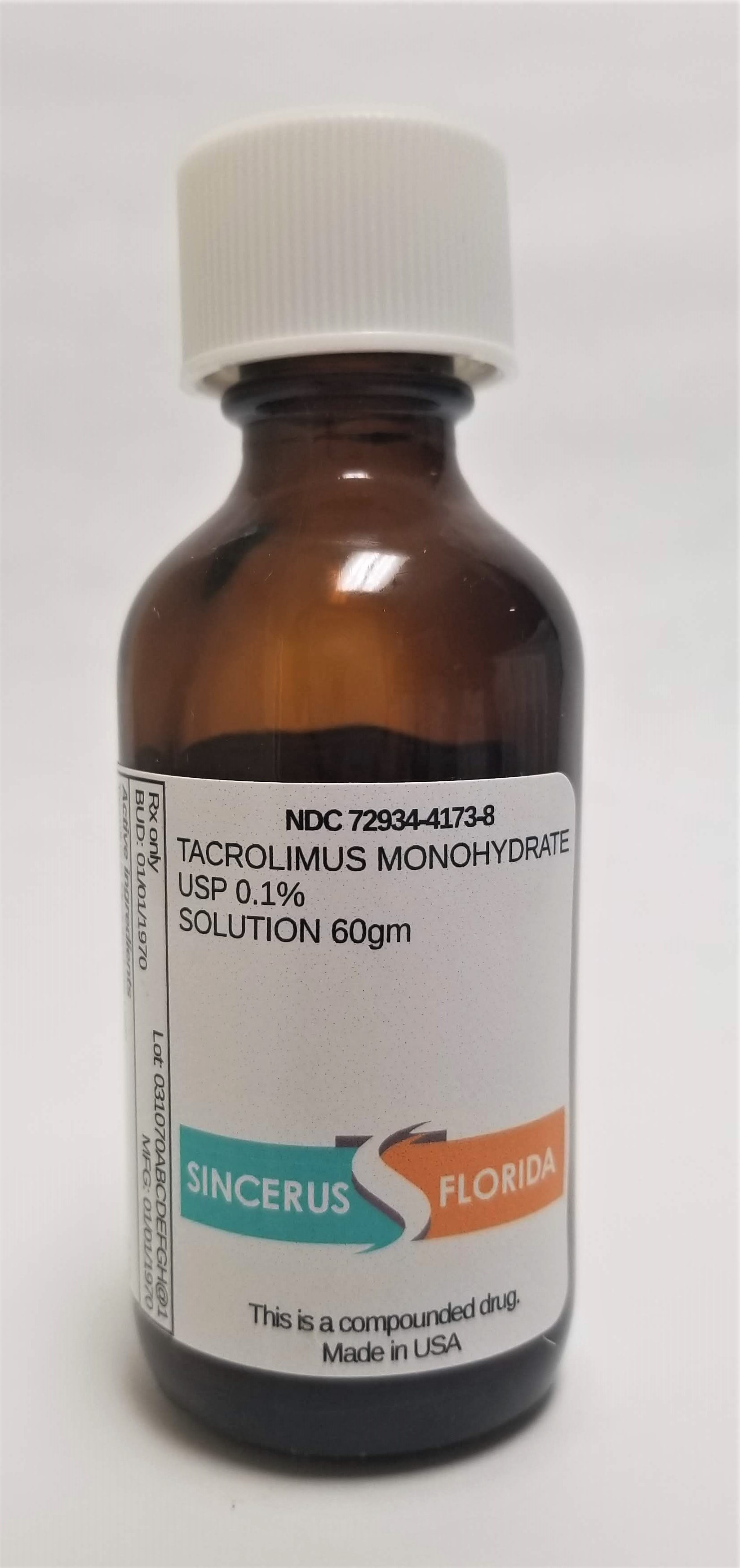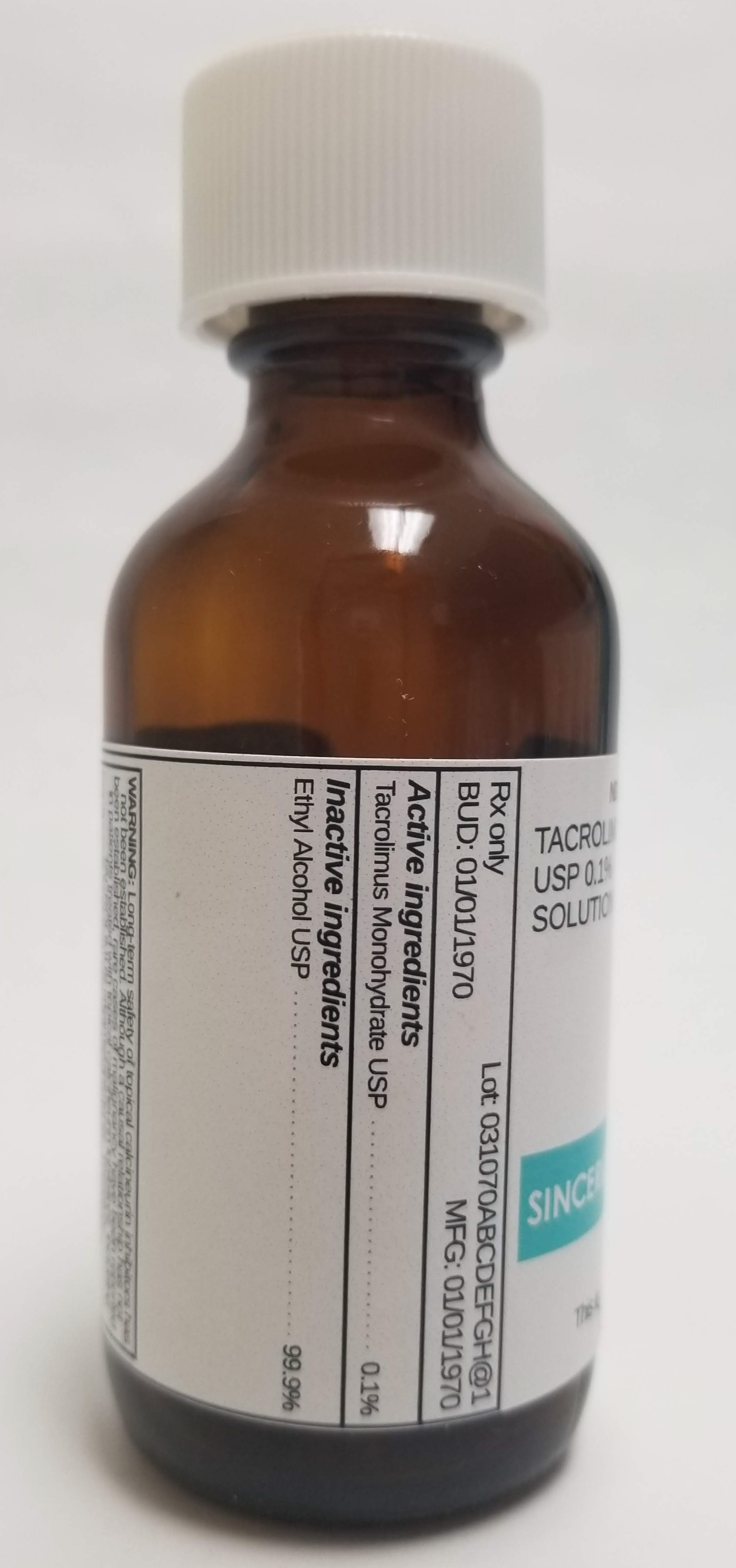 DRUG LABEL: TACROLIMUS 0.1%
NDC: 72934-4173 | Form: SOLUTION
Manufacturer: Sincerus Florida, LLC
Category: prescription | Type: HUMAN PRESCRIPTION DRUG LABEL
Date: 20190509

ACTIVE INGREDIENTS: TACROLIMUS 0.1 g/100 g

TACROLIMUS 0.1%